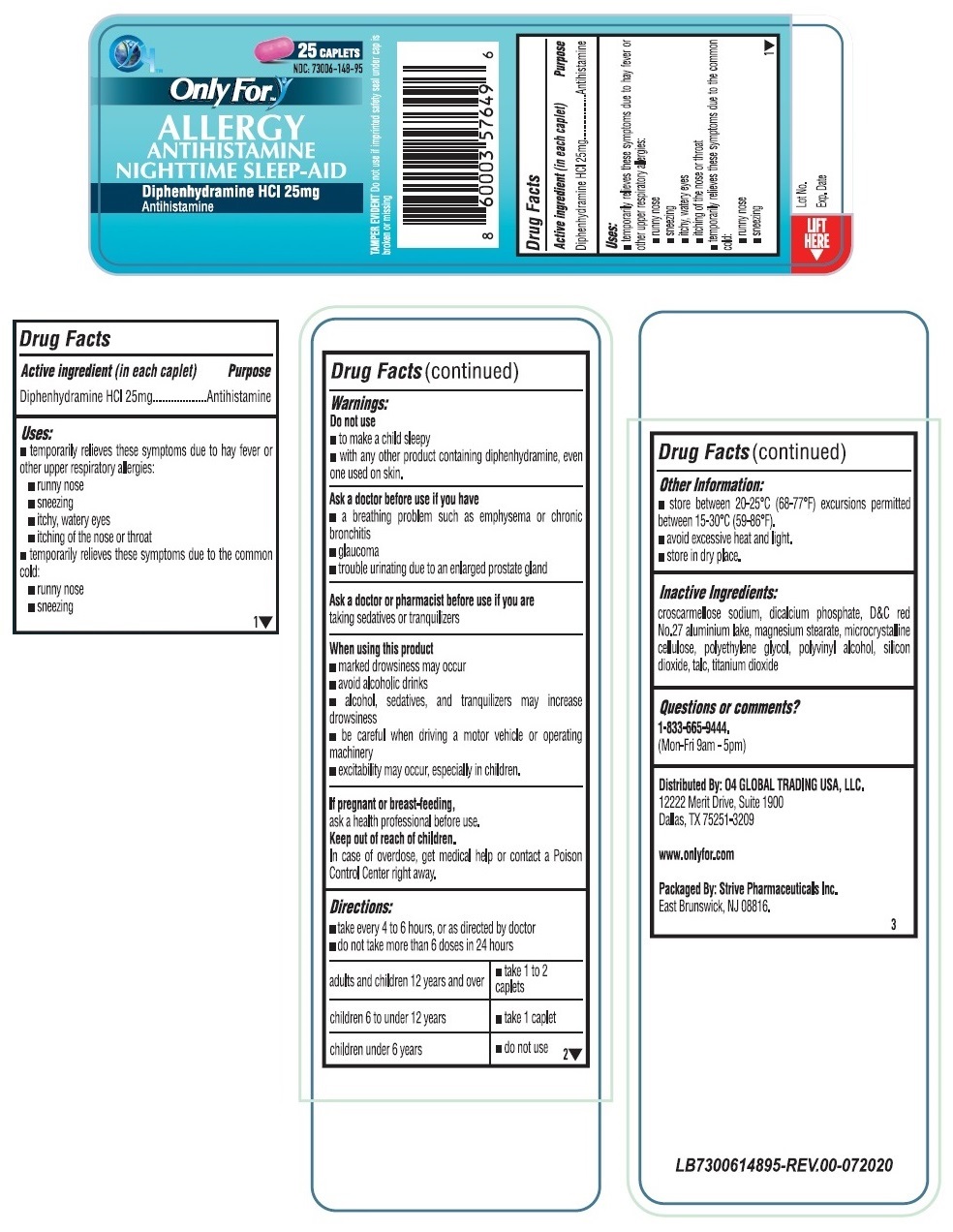 DRUG LABEL: Only For ALLERGY
NDC: 73006-148 | Form: TABLET
Manufacturer: O4 Global Trading Usa, Llc
Category: otc | Type: HUMAN OTC DRUG LABEL
Date: 20201118

ACTIVE INGREDIENTS: DIPHENHYDRAMINE HYDROCHLORIDE 25 mg/1 1
INACTIVE INGREDIENTS: CROSCARMELLOSE SODIUM; ANHYDROUS DIBASIC CALCIUM PHOSPHATE; D&C RED NO. 27 ALUMINUM LAKE; MAGNESIUM STEARATE; MICROCRYSTALLINE CELLULOSE; POLYETHYLENE GLYCOL, UNSPECIFIED; POLYVINYL ALCOHOL, UNSPECIFIED; SILICON DIOXIDE; TALC; TITANIUM DIOXIDE

Only For™ ALLERGY

Active ingredient (in each caplet)

Diphenhydramine HCl 25mg

Purpose

Antihistamine

Uses:

• temporarily relieves these symptoms due to hay fever or other upper respiratory allergies:
• runny nose
• sneezing
• itchy, watery eyes
• itching of the nose or throat

• temporarily relieves these symptoms due to the common cold:
• runny nose
• sneezing

Warnings:

Do not use
• to make a child sleepy
• with any other product containing diphenhydramine, even one used on skin.

Ask a doctor before use if you have
• a breathing problem such as emphysema or chronic bronchitis
• glaucoma
• trouble urinating due to an enlarged prostate gland

Ask a doctor or pharmacist before use if you are

taking sedatives or tranquilizers

When using this product
• marked drowsiness may occur
• avoid alcoholic drinks
• alcohol, sedatives, and tranquilizers may increase drowsiness
• be careful when driving a motor vehicle or operating machinery
• excitability may occur, especially in children.

If pregnant or breast-feeding,
ask a health professional before use.

Keep out of reach of children.
In case of overdose, get medical help or contact a Poison Control Center right away.

Directions:

• take every 4 to 6 hours, or as directed by doctor
• do not take more than 6 doses in 24 hours

adults and children 12 years and over | • take 1 to 2 caplets
children 6 to under 12 years | • take 1 caplet
children under 6 years | • do not use

Other Information:

• store between 20-25°C (68-77°F) excursions permitted between 15-30°C (59-86°F).
• avoid excessive heat and light.
• store in dry place.

Inactive Ingredients:

croscarmellose sodium, dicalcium phosphate, D&C red No.27 aluminium lake, magnesium stearate, microcrystalline cellulose, polyethylene glycol, polyvinyl alcohol, silicon dioxide, talc, titanium dioxide

Questions or comments?

1-833-665-9444.
(Mon-Fri 9am - 5pm)

ANTIHISTAMINE NIGHTTIME SLEEP-AID

TAMPER EVIDENT Do not use if imprinted safety seal under cap is broken or missing

Distributed By: O4 GLOBAL TRADING USA, LLC.
12222 Merit Drive, Suite 1900
Dallas, TX 75251-3209

www.onlyfor.com

Packaged By: Strive Pharmaceuticals Inc.
East Brunswick, NJ 08816.